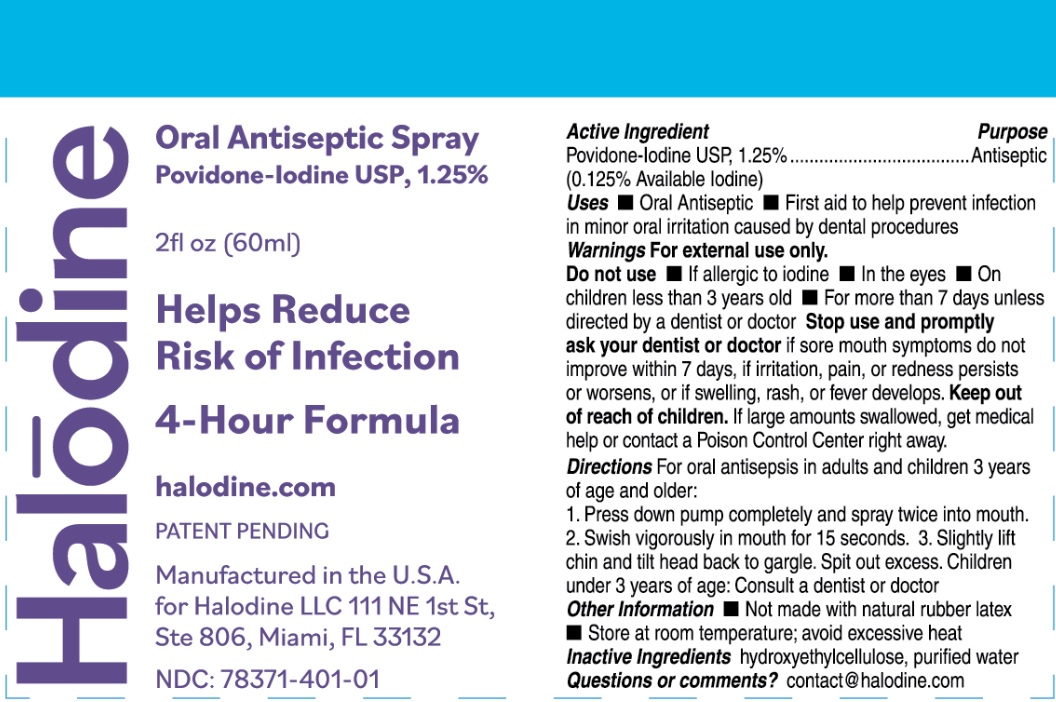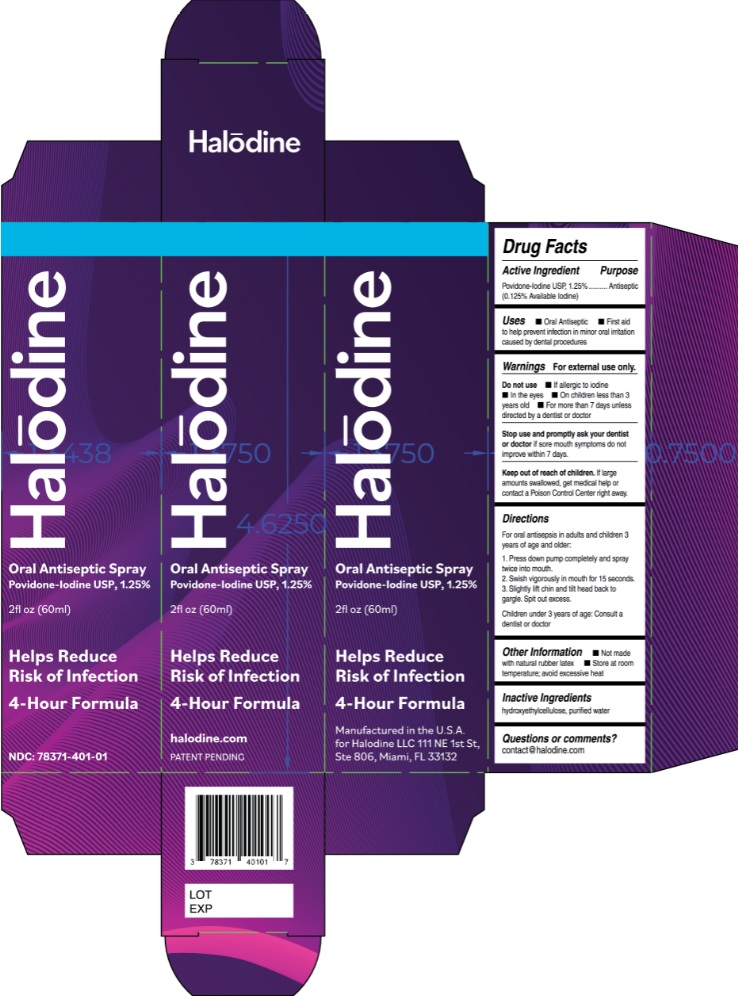 DRUG LABEL: Halodine Oral Antiseptic
NDC: 78371-401 | Form: SPRAY
Manufacturer: Halodine Llc
Category: otc | Type: HUMAN OTC DRUG LABEL
Date: 20201014

ACTIVE INGREDIENTS: POVIDONE-IODINE 1.25 g/100 mL
INACTIVE INGREDIENTS: HYDROXYETHYL CELLULOSE, UNSPECIFIED; WATER

Halodine Oral Antiseptic Spray

Active Ingredient

Povidone-Iodine USP, 1.25%

(0.125% Available Iodine)

Purpose

Antiseptic

INDICATIONS AND USAGE

Uses • Oral Antiseptic • First aid to help prevent infection in minor oral irritation caused by dental procedures

Warnings For external use only.

Do not use • If allergic to iodine • In the eyes • On children less than 3 years old • For more than 7 days unless directed by a dentist or doctor Stop use and promptly ask your dentist or doctor if sore mouth symptoms do not improve within 7 days, if irritation, pain, or redness persists or worsens, or if swelling, rash, or fever develops.

Keep out of reach of children. If large amounts swallowed, get medical help or contact a Poison Control Center right away.

DOSAGE AND ADMINISTRATION

Directions For oral antisepsis in adults and children 3 years of age and older:
1. Press down pump completely and spray twice into mouth. 2. Swish vigorously in mouth for 15 seconds. 3. Slightly lift chin and tilt head back to gargle. Spit out excess. Children under 3 years of age: Consult a dentist or doctor

Other Information • Not made with natural rubber latex • Store at room temperature; avoid excessive heat

Inactive Ingredients hydroxyethylcellulose, purified water

Questions or comments? contact@halodine.com

Povidone-Iodine USP, 1.25%

Helps Reduce Risk of Infection

4-Hour Formula

halodine.com

PATENT PENDING

Manufactured in the U.S.A.

for Halodine LLC 111 NE 1st St,

Ste 806, Miami, FL 33132